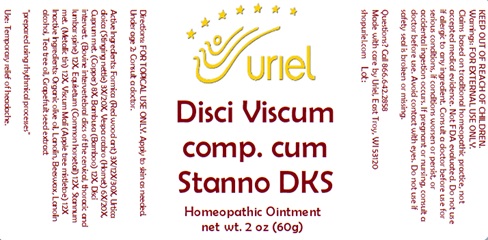 DRUG LABEL: Disci Viscum Comp.cum Stanno DKS Special Order
NDC: 48951-4181 | Form: OINTMENT
Manufacturer: Uriel Pharmacy Inc.
Category: homeopathic | Type: HUMAN OTC DRUG LABEL
Date: 20240110

ACTIVE INGREDIENTS: FORMICA RUFA 3 [hp_X]/1 g; URTICA DIOICA 3 [hp_X]/1 g; VESPA CRABRO 6 [hp_X]/1 g; COPPER 8 [hp_X]/1 g; BAMBUSA VULGARIS WHOLE 12 [hp_X]/1 g; BOS TAURUS INTERVERTEBRAL DISC 12 [hp_X]/1 g; EQUISETUM ARVENSE TOP 12 [hp_X]/1 g; TIN 12 [hp_X]/1 g; VISCUM ALBUM FRUITING TOP 12 [hp_X]/1 g
INACTIVE INGREDIENTS: TEA TREE OIL; OLIVE OIL; LANOLIN; YELLOW WAX; LANOLIN ALCOHOLS; CITRUS PARADISI SEED

Disci Viscum Comp. cum Stanno DKS

INDICATIONS AND USAGE

Directions: FOR TOPICAL USE ONLY.

DOSAGE AND ADMINISTRATION

Under age 2: Consult a doctor.

ACTIVE INGREDIENT

Active Ingredients: Formica (Red wood ant) 3X/12X/30X, Urtica dioica (Stinging nettle) 3X/20X, Vespa crabro (Hornet) 6X/20X, Cuprum met. (Copper) 8X, Bambusa (Bamboo) 12X, Disci intervert. (Bovine intervertebral discs of the cervical, thoracic and lumbar spine) 12X, Equisetum (Common horsetail) 12X, Stannum met. (Metallic tin) 12X, Viscum Mali (Apple tree mistletoe) 12X

INACTIVE INGREDIENT

Inactive Ingredients: Organic olive oil, Lanolin, Beeswax, Lanolin alcohol, Tea Tree Oil, Grapefruit seed extract

"prepared using rhythmical processes"

PURPOSE

Use: Temporary relief of headache.

KEEP OUT OF REACH OF CHILDREN.

Warnings: FOR EXTERNAL USE ONLY.
Claims based on traditional homeopathic practice, not accepted medical evidence. Not FDA evaluated. Do not use if allergic to any ingredient. Consult a doctor before use for serious conditions, if conditions worsen or persist or accidental ingestion occurs. If pregnant or nursing, consult a doctor before use. Avoid contact with eyes. Do not use if safety seal is broken or missing.

QUESTIONS

Questions? Call 866.642.2858 Made with care by Uriel, East Troy, WI 53120 shopuriel.com